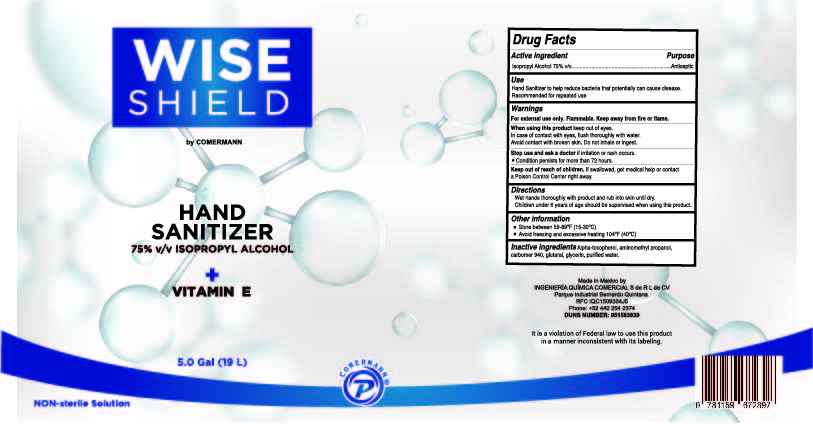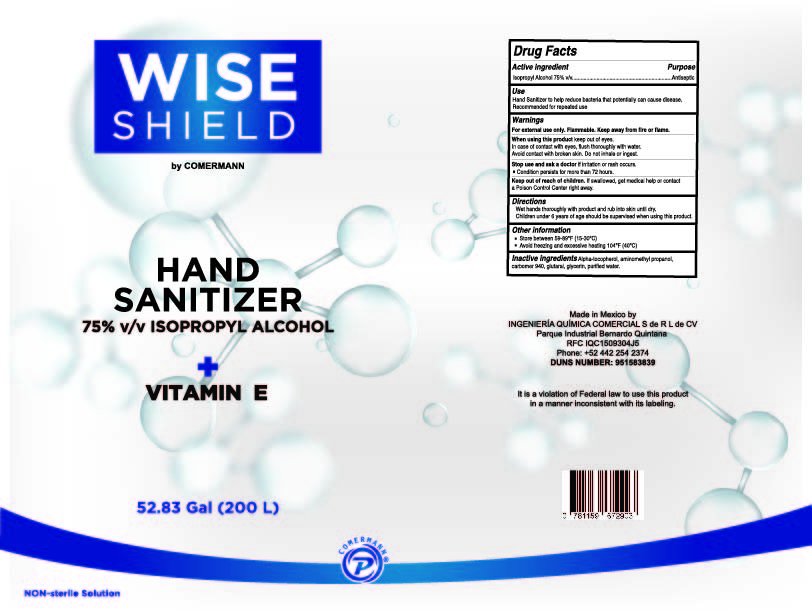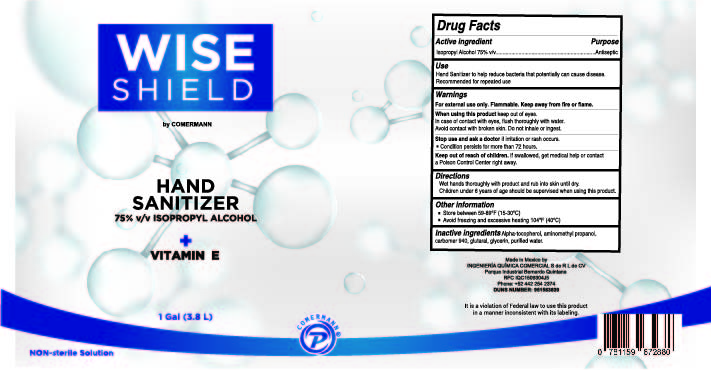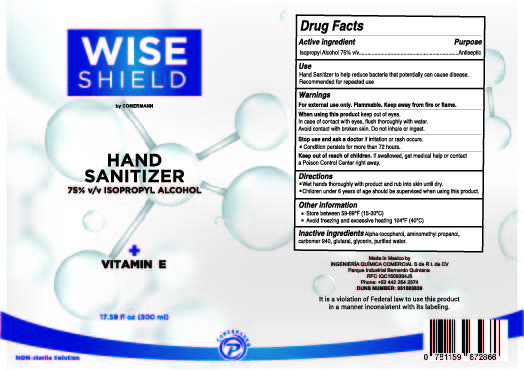 DRUG LABEL: Wise shield
NDC: 80885-001 | Form: GEL
Manufacturer: INGENIERIA QUIMICA COMERCIAL S DE RL DE CV
Category: otc | Type: HUMAN OTC DRUG LABEL
Date: 20201025

ACTIVE INGREDIENTS: ISOPROPYL ALCOHOL 75 mL/100 mL
INACTIVE INGREDIENTS: GLYCERIN 0.25 mL/100 mL; GLUTARAL 0.05 mL/100 mL; WATER; ALPHA-TOCOPHEROL 0.01 mL/100 mL; AMINOMETHYL PROPANEDIOL 0.3 mL/100 mL; CARBOMER 940 0.4 mL/100 mL

Active Ingredient(s)

Isopropyl Alcohol 75% v/v. Purpose: Antiseptic

Purpose

Antiseptic, Hand Sanitizer

Use

Hand Sanitizer to help reduce bacteria that potentially can cause disease. For use when soap and water are not available.

Warnings

For external use only. Flammable. Keep away from heat or flame

Do not use

- in children less than 2 months of age
- on open skin wounds

When using this product keep out of eyes, ears, and mouth. In case of contact with eyes, rinse eyes thoroughly with water.
Stop use and ask a doctor if irritation or rash occurs. These may be signs of a serious condition.
Keep out of reach of children. If swallowed, get medical help or contact a Poison Control Center right away.

Stop use and ask a doctor if irritation or rash occurs. These may be signs of a serious condition.

Keep out of reach of children. If swallowed, get medical help or contact a Poison Control Center right away.

Directions

- Place enough product on hands to cover all surfaces. Rub hands together until dry.
- Supervise children under 6 years of age when using this product to avoid swallowing.

Other information

- Store between 15-30C (59-86F)
- Avoid freezing and excessive heat above 40C (104F)

Inactive ingredients

Alpha-tecopherol, aminomethyl propanol, carbomer 940, glutaral, glycerin and water

Package Label - Principal Display Panel

500 ml NDC: 80885-001-01

3800 ml NDC: 80885-001-02

19000 ml NDC: 80885-001-03

200000 ml NDC: 80885-001-04